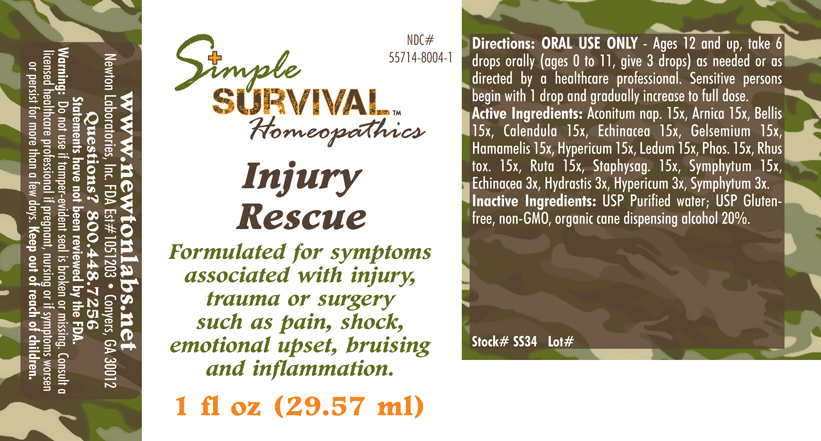 DRUG LABEL: Injury Rescue 
NDC: 55714-8004 | Form: LIQUID
Manufacturer: Newton Laboratories, Inc.
Category: homeopathic | Type: HUMAN OTC DRUG LABEL
Date: 20140415

ACTIVE INGREDIENTS: Aconitum Napellus 15 [hp_X]/1 mL; Arnica Montana 15 [hp_X]/1 mL; Bellis Perennis 15 [hp_X]/1 mL; Calendula Officinalis Flowering Top 15 [hp_X]/1 mL; Echinacea, Unspecified 15 [hp_X]/1 mL; Gelsemium Sempervirens Root 15 [hp_X]/1 mL; Hamamelis Virginiana Root Bark/stem Bark 15 [hp_X]/1 mL; Hypericum Perforatum 15 [hp_X]/1 mL; Ledum Palustre Twig 15 [hp_X]/1 mL; Phosphorus 15 [hp_X]/1 mL; Toxicodendron Pubescens Leaf 15 [hp_X]/1 mL; Ruta Graveolens Flowering Top 15 [hp_X]/1 mL; Delphinium Staphisagria Seed 15 [hp_X]/1 mL; Comfrey Root 15 [hp_X]/1 mL; Goldenseal 3 [hp_X]/1 mL
INACTIVE INGREDIENTS: Alcohol

Injury Rescue

INDICATIONS & USAGE SECTION

Injury Rescue Formulated for symptoms associated with injury, trauma or surgery such as pain, shock, emotional upset, bruising and inflammation.

DOSAGE & ADMINISTRATION SECTION

Directions: ORAL USE ONLY - Ages 12 and up, take 6 drops orally (ages 0 to 11, give 3 drops) as needed or as directed by a healthcare professional. Sensitive persons begin with 1 drop and gradually increase to full dose.

OTC - ACTIVE INGREDIENT SECTION

Aconitum nap. 15x, Arnica 15x, Bellis 15x, Calendula 15x, Echinacea 15x, Gelsemium 15x, Hamamelis 15x, Hypericum 15x, Ledum 15x, Phos. 15x, Rhus tox. 15x, Ruta 15x, Staphysag. 15x, Symphytum 15x, Echinacea 3x, Hydrastis 3x, Hypericum 3x, Symphytum 3x.

OTC - PURPOSE SECTION

Formulated for symptoms associated with injury, trauma or surgery such as pain, shock, emotional upset, bruising and inflammation.

INACTIVE INGREDIENT SECTION

Inactive Ingredients: USP Purified Water; USP Gluten-free, non-GMO, organic cane dispensing alcohol 20%.

QUESTIONS

www.newtonlabs.net Newton Laboratories, Inc. FDA Est # 1051203 - Conyers, GA 30012
Questions? 1.800.448.7256

WARNINGS SECTION

Warning: Do not use if tamper - evident seal is broken or missing. Consult a licensed healthcare professional if pregnant, nursing or if symptoms worsen or persist for more than a few days. Keep out of reach of children.

OTC - PREGNANCY OR BREAST FEEDING SECTION

Consult a licensed healthcare professional if pregnant, nursing or if symptoms worsen or persist for more than a few days.

OTC - KEEP OUT OF REACH OF CHILDREN SECTION

Keep out of reach of children.